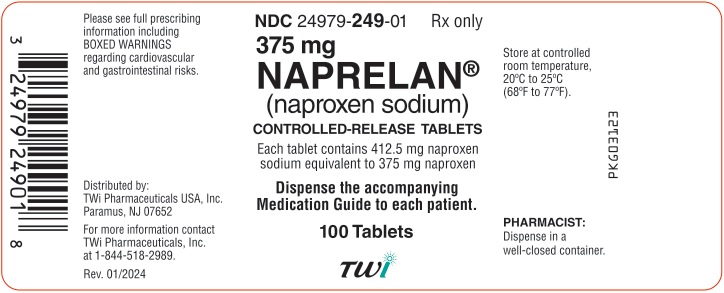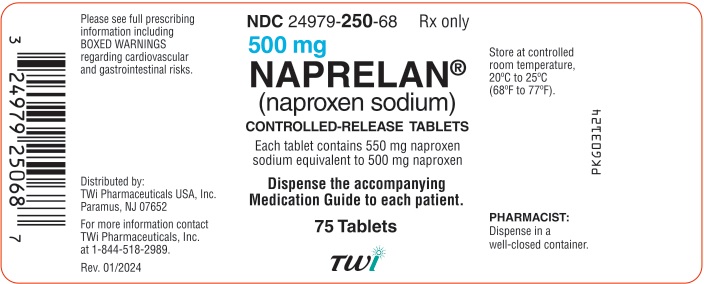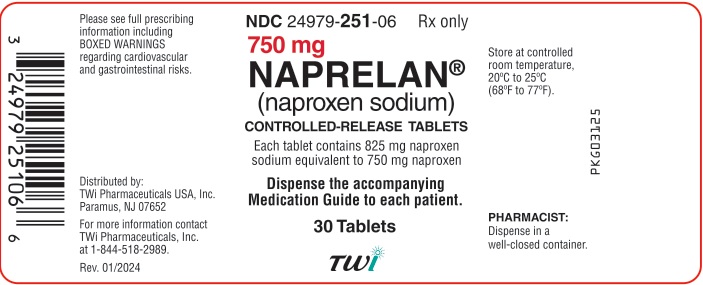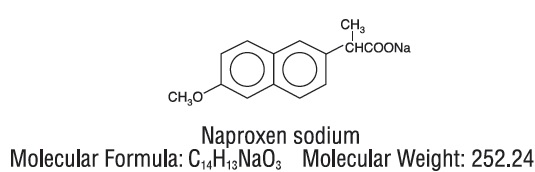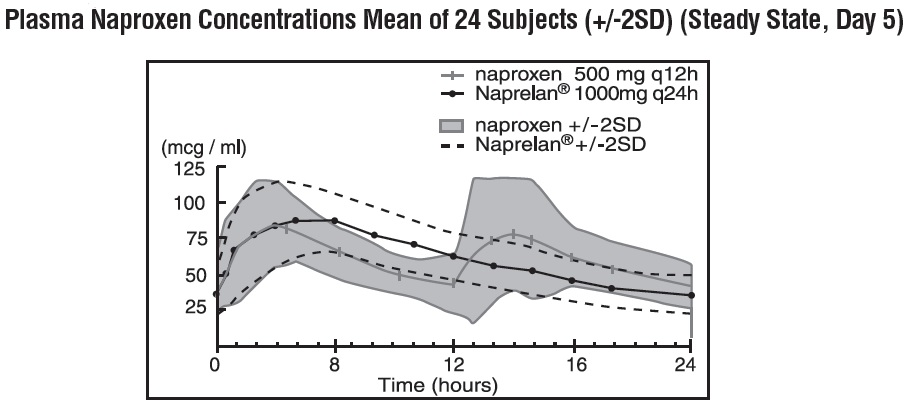 DRUG LABEL: Naprelan
NDC: 24979-249 | Form: TABLET, FILM COATED, EXTENDED RELEASE
Manufacturer: Upsher-Smith Laboratories, LLC
Category: prescription | Type: HUMAN PRESCRIPTION DRUG LABEL
Date: 20260108

ACTIVE INGREDIENTS: NAPROXEN SODIUM 375 mg/1 1
INACTIVE INGREDIENTS: AMMONIO METHACRYLATE COPOLYMER TYPE A; AMMONIO METHACRYLATE COPOLYMER TYPE B; CITRIC ACID MONOHYDRATE; CROSPOVIDONE (120 .MU.M); MAGNESIUM STEARATE; METHACRYLIC ACID - METHYL METHACRYLATE COPOLYMER (1:1); MICROCRYSTALLINE CELLULOSE; POVIDONE, UNSPECIFIED; TALC; HYPROMELLOSE, UNSPECIFIED; POLYETHYLENE GLYCOL, UNSPECIFIED; TITANIUM DIOXIDE

HIGHLIGHTS OF PRESCRIBING INFORMATION

These highlights do not include all the information needed to use NAPRELAN® safely and effectively. See full prescribing information for NAPRELAN®.
NAPRELAN (naproxen sodium) Controlled-Release Tablets, for oral use
Initial U.S. Approval: 1976

RECENT MAJOR CHANGES

Warnings and Precautions (5.9) 11/2024

WARNING: RISK OF SERIOUS CARDIOVASCULAR AND GASTROINTESTINAL EVENTS

See full prescribing information for complete boxed warning.

- Nonsteroidal anti-inflammatory drugs (NSAIDs) cause an increased risk of serious cardiovascular thrombotic events, including myocardial infarction and stroke, which can be fatal. This risk may occur early in treatment and may increase with duration of use (5.1)
- NAPRELAN® is contraindicated in the setting of coronary artery bypass graft (CABG) surgery (4, 5.1)
- NSAIDs cause an increased risk of serious gastrointestinal (GI) adverse events including bleeding, ulceration, and perforation of the stomach or intestines, which can be fatal. These events can occur at any time during use and without warning symptoms. Elderly patients and patients with a prior history of peptic ulcer disease and/or GI bleeding are at greater risk for serious GI events (5.2)

1 INDICATIONS AND USAGE

NAPRELAN is a nonsteroidal anti-inflammatory drug indicated for the treatment of:

• rheumatoid arthritis (RA)(1)
• osteoarthritis (OA)(1)
• ankylosing spondylitis (AS)(1)
• tendinitis, bursitis (1)
• acute gout (1)
• primary dysmenorrhea (PD) (1)
• the relief of mild to moderate pain (1)

2 DOSAGE AND ADMINISTRATION

- Use the lowest effective dosage for shortest duration consistent with individual patient treatment goals (2)
- RA, OA, and AS: The dosage is two 375 mg or 500 mg tablets once daily, or one 750 mg tablet once daily.
- Management of Pain, PD, and Acute Tendinitis and Bursitis: The dosage is two 500 mg tablets once daily. For patients requiring greater analgesic benefit, two 750 mg tablets or three 500 mg tablets may be used for a limited period. Thereafter, the total daily dose should not exceed two 500 mg tablets
- For the treatment of Acute Gout: The dosage is two to three 500 mg tablets once daily on the first day, followed by two 500 mg tablets once daily, until the attack has subsided.

3 DOSAGE FORMS AND STRENGTHS

NAPRELAN (naproxen sodium) Controlled-Release Tablets: 375 mg, 500 mg, and 750 mg (3)

4 CONTRAINDICATIONS

- Known hypersensitivity to naproxen or any components of the drug product (4)
- History of asthma, urticaria, or other allergic-type reactions after taking aspirin or other NSAIDs (4)
- In the setting of CABG surgery (4)

5 WARNINGS AND PRECAUTIONS

- Hepatotoxicity: Inform patients of warning signs and symptoms of hepatotoxicity. Discontinue if abnormal liver tests persist or worsen or if clinical signs and symptoms of liver disease develop (5.3)
- Hypertension: Patients taking some antihypertensive medications may have impaired response to these therapies when taking NSAIDs. Monitor blood pressure (5.4, 7)
- Heart Failure and Edema: Avoid use of NAPRELAN in patients with severe heart failure unless benefits are expected to outweigh risk of worsening heart failure (5.5)
- Renal Toxicity: Monitor renal function in patients with renal or hepatic impairment, heart failure, dehydration, or hypovolemia. Avoid use of NAPRELAN in patients with advanced renal disease unless benefits are expected to outweigh risk of worsening renal function (5.6)
- Anaphylactic Reactions: Seek emergency help if an anaphylactic reaction occurs (5.7)
- Exacerbation of Asthma Related to Aspirin Sensitivity: NAPRELAN is contraindicated in patients with aspirin-sensitive asthma. Monitor patients with preexisting asthma (without aspirin sensitivity) (5.8)
- Serious Skin Reactions: Discontinue NAPRELAN at first appearance of skin rash or other signs of hypersensitivity (5.9)
- Drug Reaction with Eosinophilia and Systemic Symptoms (DRESS): Discontinue and evaluate clinically (5.10).
- Fetal Toxicity: Limit use of NSAIDs, including NAPRELAN, between about 20 to 30 weeks in pregnancy due to the risk of oligohydramnios/fetal renal dysfunction. Avoid use of NSAIDs in women at about 30 weeks gestation and later in pregnancy due to the risks of oligohydramnios/fetal renal dysfunction and premature closure of the fetal ductus arteriosus (5.11, 8.1).
- Hematologic Toxicity: Monitor hemoglobin or hematocrit in patients with any signs or symptoms of anemia (5.12, 7)

6 ADVERSE REACTIONS

The most frequent adverse events were headache (15%), followed by dyspepsia (14%), and flu syndrome (10%). (6.1)

To report SUSPECTED ADVERSE REACTIONS, contact TWi Pharmaceuticals, Inc. at 1-844-518-2989 or FDA at 1-800-FDA-1088 or www.fda.gov/medwatch.

7 DRUG INTERACTIONS

- Drugs that Interfere with Hemostasis (e.g. warfarin, aspirin, SSRIs/SNRIs): Monitor patients for bleeding who are concomitantly taking NAPRELAN with drugs that interfere with hemostasis. Concomitant use of NAPRELAN and analgesic doses of aspirin is not generally recommended (7)
- ACE Inhibitors, Angiotensin Receptor Blockers (ARB), or Beta-Blockers: Concomitant use with NAPRELAN may diminish the antihypertensive effect of these drugs. Monitor blood pressure (7)
- ACE Inhibitors and ARBs: Concomitant use with NAPRELAN in elderly, volume depleted, or those with renal impairment may result in deterioration of renal function. In such high risk patients, monitor for signs of worsening renal function (7)
- Diuretics: NSAIDs can reduce natriuretic effect of furosemide and thiazide diuretics. Monitor patients to assure diuretic efficacy including antihypertensive effects (7)
- Digoxin: Concomitant use with NAPRELAN can increase serum concentration and prolong half-life of digoxin. Monitor serum digoxin levels (7)

8 USE IN SPECIFIC POPULATIONS

Infertility: NSAIDs are associated with reversible infertility. Consider withdrawal of NAPRELAN in women who have difficulties conceiving (8.3)

FULL PRESCRIBING INFORMATION

WARNING: RISK OF SERIOUS CARDIOVASCULAR AND GASTROINTESTINAL EVENTS

Cardiovascular Thrombotic Events

- Nonsteroidal anti-inflammatory drugs (NSAIDs) cause an increased risk of serious cardiovascular thrombotic events, including myocardial infarction and stroke, which can be fatal. This risk may occur early in treatment and may increase with duration of use [see Warnings and Precautions (5.1)].
- NAPRELAN is contraindicated in the setting of coronary artery bypass graft (CABG) surgery [see Contraindications (4) and Warnings and Precautions (5.1)].

Gastrointestinal Bleeding, Ulceration, and Perforation

- NSAIDs cause an increased risk of serious gastrointestinal (GI) adverse events including bleeding, ulceration, and perforation of the stomach or intestines, which can be fatal. These events can occur at any time during use and without warning symptoms. Elderly patients and patients with a prior history of peptic ulcer disease and/or GI bleeding are at greater risk for serious GI events [see Warnings and Precautions (5.2)].

1 INDICATIONS AND USAGE

NAPRELAN Tablets are indicated for the treatment of:

• rheumatoid arthritis (RA)
• osteoarthritis (OA)
• ankylosing spondylitis (AS)
• tendinitis, bursitis
• acute gout
• primary dysmenorrhea (PD)
• the relief of mild to moderate pain

[see Warnings and Precautions (5)].

2 DOSAGE AND ADMINISTRATION

2.1 General Dosing Instructions

Carefully consider the potential benefits and risks of NAPRELAN and other treatment options before deciding to use NAPRELAN. Use the lowest effective dosage for the shortest duration consistent with individual patient treatment goals [see Warnings and Precautions (5)].

After observing the response to initial therapy with NAPRELAN, the dose and frequency should be adjusted to suit an individual patient’s needs.

2.2 Rheumatoid Arthritis, Osteoarthritis, and Ankylosing Spondylitis

The recommended starting dose of NAPRELAN Tablets in adults is two NAPRELAN 375 mg tablets (750 mg) once daily, one NAPRELAN 750 mg (750 mg) once daily, or two NAPRELAN 500 mg tablets (1,000 mg) once daily. Patients already taking naproxen 250 mg, 375 mg, or 500 mg twice daily (morning and evening) may have their total daily dose replaced with NAPRELAN Tablets as a single daily dose.

During long-term administration, the dose of NAPRELAN Tablets may be adjusted up or down depending on the clinical response of the patient. In patients who tolerate lower doses of NAPRELAN Tablets well, the dose may be increased to two NAPRELAN 750 mg tablets (1,500 mg), or three NAPRELAN 500 mg tablets (1,500 mg) once daily for limited periods when a higher level of anti-inflammatory/analgesic activity is required. When treating patients, especially at the higher dose levels, the physician should observe sufficient increased clinical benefit to offset the potential increased risk [see Clinical Pharmacology (12.3)]. The lowest effective dose should be sought and used in every patient. Symptomatic improvement in arthritis usually begins within one week; however, treatment for two weeks may be required to achieve a therapeutic benefit.

2.3 Management of Pain, Primary Dysmenorrhea, and Acute Tendinitis and Bursitis

The recommended starting dose is two NAPRELAN 500 mg tablets (1,000 mg) once daily. For patients requiring greater analgesic benefit, two NAPRELAN 750 mg tablets (1,500 mg) or three NAPRELAN 500 mg tablets (1,500 mg) may be used for a limited period. Thereafter, the total daily dose should not exceed two NAPRELAN 500 mg tablets (1,000 mg).

2.4 Acute Gout

The recommended dose on the first day is two to three NAPRELAN 500 mg tablets (1,000 to 1,500 mg) once daily, followed by two NAPRELAN 500 mg tablets (1,000 mg) once daily, until the attack has subsided.

2.5 Dosage Adjustments in Patients with Hepatic Impairment

A lower dose should be considered in patients with renal or hepatic impairment or in elderly patients [see Warnings and Precautions (5.3)]. Studies indicate that although total plasma concentration of naproxen is unchanged, the unbound plasma fraction of naproxen is increased in the elderly. Caution is advised when high doses are required and some adjustment of dosage may be required in elderly patients. As with other drugs used in the elderly it is prudent to use the lowest effective dose.

3 DOSAGE FORMS AND STRENGTHS

NAPRELAN (naproxen sodium) Controlled-Release Tablets are available as follows:

NAPRELAN 375: white, capsule-shaped tablet with “N” on one side and “375” on the reverse. Each tablet contains 412.5 mg naproxen sodium equivalent to 375 mg naproxen.

NAPRELAN 500: white, capsule-shaped tablet with “N” on one side and “500” on the reverse. Each tablet contains 550 mg naproxen sodium equivalent to 500 mg naproxen.

NAPRELAN 750: white, capsule-shaped tablet with “N” on one side and “750” on the reverse. Each tablet contains 825 mg naproxen sodium equivalent to 750 mg naproxen.

4 CONTRAINDICATIONS

NAPRELAN is contraindicated in the following patients:

- Known hypersensitivity (e.g., anaphylactic reactions and serious skin reactions) to naproxen or any components of the drug product [see Warnings and Precautions (5.7, 5.9)]
- History of asthma, urticaria, or other allergic-type reactions after taking aspirin or other NSAIDs. Severe, sometimes fatal, anaphylactic reactions to NSAIDs have been reported in such patients [see Warnings and Precautions (5.7, 5.8)]
- In the setting of coronary artery bypass graft (CABG) surgery [see Warnings and Precautions (5.1)]

5 WARNINGS AND PRECAUTIONS

5.1 Cardiovascular Thrombotic Events

Clinical trials of several COX-2 selective and nonselective NSAIDs of up to three years duration have shown an increased risk of serious cardiovascular (CV) thrombotic events, including myocardial infarction (MI) and stroke, which can be fatal. Based on available data, it is unclear that the risk for CV thrombotic events is similar for all NSAIDs. The relative increase in serious CV thrombotic events over baseline conferred by NSAID use appears to be similar in those with and without known CV disease or risk factors for CV disease. However, patients with known CV disease or risk factors had a higher absolute incidence of excess serious CV thrombotic events, due to their increased baseline rate. Some observational studies found that this increased risk of serious CV thrombotic events began as early as the first weeks of treatment. The increase in CV thrombotic risk has been observed most consistently at higher doses.

To minimize the potential risk for an adverse CV event in NSAID-treated patients, use the lowest effective dose for the shortest duration possible. Physicians and patients should remain alert for the development of such events, throughout the entire treatment course, even in the absence of previous CV symptoms. Patients should be informed about the symptoms of serious CV events and the steps to take if they occur.

There is no consistent evidence that concurrent use of aspirin mitigates the increased risk of serious CV thrombotic events associated with NSAID use. The concurrent use of aspirin and an NSAID, such as naproxen, increases the risk of serious gastrointestinal (GI) events [see Warnings and Precautions (5.2)].

Status Post Coronary Artery Bypass Graft (CABG) Surgery Two large, controlled clinical trials of a COX-2 selective NSAID for the treatment of pain in the first 10-14 days following CABG surgery found an increased incidence of myocardial infarction and stroke. NSAIDs are contraindicated in the setting of CABG [see Contraindications (4)].

Post-MI PatientsObservational studies conducted in the Danish National Registry have demonstrated that patients treated with NSAIDs in the post-MI period were at increased risk of reinfarction, CV-related death, and all-cause mortality beginning in the first week of treatment. In this same cohort, the incidence of death in the first year post-MI was 20 per 100 person years in NSAID-treated patients compared to 12 per 100 person years in non-NSAID exposed patients. Although the absolute rate of death declined somewhat after the first year post-MI, the increased relative risk of death in NSAID users persisted over at least the next four years of follow-up.

Avoid the use of NAPRELAN in patients with a recent MI unless the benefits are expected to outweigh the risk of recurrent CV thrombotic events. If NAPRELAN is used in patients with a recent MI, monitor patients for signs of cardiac ischemia.

5.2 Gastrointestinal Bleeding, Ulceration, and Perforation

NSAIDs, including naproxen, cause serious gastrointestinal (GI) adverse events including inflammation, bleeding, ulceration, and perforation of the esophagus, stomach, small intestine, or large intestine, which can be fatal. These serious adverse events can occur at any time, with or without warning symptoms, in patients treated with NSAIDs. Only one in five patients who develop a serious upper GI adverse event on NSAID therapy is symptomatic. Upper GI ulcers, gross bleeding, or perforation caused by NSAIDs occurred in approximately 1% of patients treated for 3 to 6 months, and in about 2% to 4% of patients treated for one year. However, even short-term NSAID therapy is not without risk.

Risk Factors for GI Bleeding, Ulceration, and PerforationPatients with a prior history of peptic ulcer disease and/or GI bleeding who used NSAIDs had a greater than 10-fold increased risk for developing a GI bleed compared to patients without these risk factors. Other factors that increase the risk of GI bleeding in patients treated with NSAIDs include longer duration of NSAID therapy; concomitant use of oral corticosteroids, aspirin, anticoagulants, or selective serotonin reuptake inhibitors (SSRIs); smoking; use of alcohol; older age; and poor general health status. Most postmarketing reports of fatal GI events occurred in elderly or debilitated patients. Additionally, patients with advanced liver disease and/or coagulopathy are at increased risk for GI bleeding.

Strategies to Minimize the GI Risks in NSAID-treated patients:

- Use the lowest effective dosage for the shortest possible duration.
- Avoid administration of more than one NSAID at a time.
- Avoid use in patients at higher risk unless benefits are expected to outweigh the increased risk of bleeding. For such patients, as well as those with active GI bleeding, consider alternate therapies other than NSAIDs.
- Remain alert for signs and symptoms of GI ulceration and bleeding during NSAID therapy.
- If a serious GI adverse event is suspected, promptly initiate evaluation and treatment, and discontinue NAPRELAN until a serious GI adverse event is ruled out.
- In the setting of concomitant use of low-dose aspirin for cardiac prophylaxis, monitor patients more closely for evidence of GI bleeding [see Drug Interactions (7)].

5.3 Hepatotoxicity

Elevations of ALT or AST (three or more times the upper limit of normal [ULN]) have been reported in approximately 1% of NSAID-treated patients in clinical trials. In addition, rare, sometimes fatal, cases of severe hepatic injury, including fulminant hepatitis, liver necrosis, and hepatic failure have been reported.

Elevations of ALT or AST (less than three times ULN) may occur in up to 15% of patients treated with NSAIDs including naproxen.

Inform patients of the warning signs and symptoms of hepatotoxicity (e.g., nausea, fatigue, lethargy, diarrhea, pruritus, jaundice, right upper quadrant tenderness, and "flu-like" symptoms). If clinical signs and symptoms consistent with liver disease develop, or if systemic manifestations occur (e.g., eosinophilia, rash, etc.), discontinue NAPRELAN immediately, and perform a clinical evaluation of the patient.

5.4 Hypertension

NSAIDs, including NAPRELAN, can lead to new onset or worsening of pre-existing hypertension, either of which may contribute to the increased incidence of CV events. Patients taking angiotensin converting enzyme (ACE) inhibitors, thiazide diuretics, or loop diuretics may have impaired response to these therapies when taking NSAIDs [see Drug Interactions (7)].

Monitor blood pressure (BP) during the initiation of NSAID treatment and throughout the course of therapy.

5.5 Heart Failure and Edema

The Coxib and traditional NSAID Trialists’ Collaboration meta-analysis of randomized controlled trials demonstrated an approximately two-fold increase in hospitalizations for heart failure in COX-2 selective-treated patients and nonselective NSAID-treated patients compared to placebo-treated patients. In a Danish National Registry study of patients with heart failure, NSAID use increased the risk of MI, hospitalization for heart failure, and death.

Additionally, fluid retention and edema have been observed in some patients treated with NSAIDs. Use of naproxen may blunt the CV effects of several therapeutic agents used to treat these medical conditions (e.g., diuretics, ACE inhibitors, or angiotensin receptor blockers [ARBs]) [see Drug Interactions (7)].

Avoid the use of NAPRELAN in patients with severe heart failure unless the benefits are expected to outweigh the risk of worsening heart failure. If NAPRELAN is used in patients with severe heart failure, monitor patients for signs of worsening heart failure.

5.6 Renal Toxicity and Hyperkalemia

Renal ToxicityLong-term administration of NSAIDs has resulted in renal papillary necrosis and other renal injury.

Renal toxicity has also been seen in patients in whom renal prostaglandins have a compensatory role in the maintenance of renal perfusion. In these patients, administration of an NSAID may cause a dose-dependent reduction in prostaglandin formation and, secondarily, in renal blood flow, which may precipitate overt renal decompensation. Patients at greatest risk of this reaction are those with impaired renal function, dehydration, hypovolemia, heart failure, liver dysfunction, those taking diuretics and ACE inhibitors or ARBs, and the elderly. Discontinuation of NSAID therapy is usually followed by recovery to the pretreatment state.

No information is available from controlled clinical studies regarding the use of NAPRELAN in patients with advanced renal disease. The renal effects of NAPRELAN may hasten the progression of renal dysfunction in patients with preexisting renal disease.

Correct volume status in dehydrated or hypovolemic patients prior to initiating NAPRELAN. Monitor renal function in patients with renal or hepatic impairment, heart failure, dehydration, or hypovolemia during use of NAPRELAN [see Drug Interactions (7)]. Avoid the use of NAPRELAN in patients with advanced renal disease unless the benefits are expected to outweigh the risk of worsening renal function. If NAPRELAN is used in patients with advanced renal disease, monitor patients for signs of worsening renal function.

Hyperkalemia
Increases in serum potassium concentration, including hyperkalemia, have been reported with use of NSAIDs, even in some patients without renal impairment. In patients with normal renal function, these effects have been attributed to a hyporeninemic-hypoaldosteronism state.

5.7 Anaphylactic Reactions

Naproxen has been associated with anaphylactic reactions in patients with and without known hypersensitivity to naproxen and in patients with aspirin-sensitive asthma [see Contraindications (4) and Warnings and Precautions (5.8)].

Seek emergency help if an anaphylactic reaction occurs.

5.8 Exacerbation of Asthma Related to Aspirin Sensitivity

A subpopulation of patients with asthma may have aspirin-sensitive asthma which may include chronic rhinosinusitis complicated by nasal polyps; severe, potentially fatal bronchospasm; and/or intolerance to aspirin and other NSAIDs. Because cross-reactivity between aspirin and other NSAIDs has been reported in such aspirin-sensitive patients, NAPRELAN is contraindicated in patients with this form of aspirin sensitivity [see Contraindications (4)]. When NAPRELAN is used in patients with preexisting asthma (without known aspirin sensitivity), monitor patients for changes in the signs and symptoms of asthma.

5.9 Serious Skin Reactions

NSAIDs, including naproxen can cause serious skin adverse reactions such as exfoliative dermatitis, Stevens-Johnson Syndrome (SJS), and toxic epidermal necrolysis (TEN), which can be fatal. NSAIDs can also cause fixed drug eruption (FDE). FDE may present as a more severe variant known as generalized bullous fixed drug eruption (GBFDE), which can be life-threatening. These serious events may occur without warning. Inform patients about the signs and symptoms of serious skin reactions, and to discontinue the use of NAPRELAN at the first appearance of skin rash or any other sign of hypersensitivity.

NAPRELAN is contraindicated in patients with previous serious skin reactions to NSAIDs [see Contraindications (4)].

5.10 Drug Reaction with Eosinophilia and Systemic Symptoms (DRESS)

Drug Reaction with Eosinophilia and Systemic Symptoms (DRESS) has been reported in patients taking NSAIDs such as NAPRELAN. Some of these events have been fatal or life-threatening. DRESS typically, although not exclusively, presents with fever, rash, lymphadenopathy, and/or facial swelling. Other clinical manifestations may include hepatitis, nephritis, hematological abnormalities, myocarditis, or myositis. Sometimes symptoms of DRESS may resemble an acute viral infection. Eosinophilia is often present. Because this disorder is variable in its presentation, other organ systems not noted here may be involved. It is important to note that early manifestations of hypersensitivity, such as fever or lymphadenopathy, may be present even though rash is not evident. If such signs or symptoms are present, discontinue NAPRELAN and evaluate the patient immediately.

5.11 Fetal Toxicity

Premature Closure of Fetal Ductus Arteriosus

Avoid use of NSAIDs, including NAPRELAN, in pregnant women at about 30 weeks gestation and later. NSAIDs, including NAPRELAN, increase the risk of premature closure of the fetal ductus arteriosus at approximately this gestational age.

Oligohydramnios/Neonatal Renal Impairment

Use of NSAIDs, including NAPRELAN, at about 20 weeks gestation or later in pregnancy may cause fetal renal dysfunction leading to oligohydramnios and, in some cases, neonatal renal impairment. These adverse outcomes are seen, on average, after days to weeks of treatment, although oligohydramnios has been infrequently reported as soon as 48 hours after NSAID initiation. Oligohydramnios is often, but not always, reversible with treatment discontinuation. Complications of prolonged oligohydramnios may, for example, include limb contractures and delayed lung maturation. In some postmarketing cases of impaired neonatal renal function, invasive procedures such as exchange transfusion or dialysis were required.

If NSAID treatment is necessary between about 20 weeks and 30 weeks gestation, limit NAPRELAN use to the lowest effective dose and shortest duration possible. Consider ultrasound monitoring of amniotic fluid if NAPRELAN treatment extends beyond 48 hours. Discontinue NAPRELAN if oligohydramnios occurs and follow up according to clinical practice [see Use in Specific Populations (8.1)].

5.12 Hematologic Toxicity

Anemia has occurred in NSAID-treated patients. This may be due to occult or gross blood loss, fluid retention, or an incompletely described effect on erythropoiesis. If a patient treated with NAPRELAN has any signs or symptoms of anemia, monitor hemoglobin or hematocrit.

NSAIDs, including NAPRELAN, may increase the risk of bleeding events. Co-morbid conditions such as coagulation disorders, concomitant use of warfarin, other anticoagulants, antiplatelet agents (e.g., aspirin), serotonin reuptake inhibitors (SSRIs) and serotonin norepinephrine reuptake inhibitors (SNRIs) may increase this risk. Monitor these patients for signs of bleeding [see Drug Interactions (7)].

5.13 Masking of Inflammation and Fever

The pharmacological activity of NAPRELAN in reducing inflammation, and possibly fever, may diminish the utility of diagnostic signs in detecting infections.

5.14 Laboratory Monitoring

Because serious GI bleeding, hepatotoxicity, and renal injury can occur without warning symptoms or signs, consider monitoring patients on long-term NSAID treatment with a CBC and a chemistry profile periodically [see Warnings and Precautions (5.2, 5.3, 5.6)].

6 ADVERSE REACTIONS

The following adverse reactions are discussed in greater detail in other sections of the labeling:

- Cardiovascular Thrombotic Events [see Warnings and Precautions (5.1)]
- GI Bleeding, Ulceration and Perforation [see Warnings and Precautions (5.2)]
- Hepatotoxicity [see Warnings and Precautions (5.3)]
- Hypertension [see Warnings and Precautions (5.4)]
- Heart Failure and Edema [see Warnings and Precautions (5.5)]
- Renal Toxicity and Hyperkalemia [see Warnings and Precautions (5.6)]
- Anaphylactic Reactions [see Warnings and Precautions (5.7)]
- Serious Skin Reactions [see Warnings and Precautions (5.9)]
- Hematologic Toxicity [see Warnings and Precautions (5.12)]

6.1 Clinical Trials Experience

Because clinical trials are conducted under widely varying conditions, adverse reaction rates observed in the clinical trials of a drug cannot be directly compared to rates in the clinical trials of another drug and may not reflect the rates observed in practice.

As with all drugs in this class, the frequency and severity of adverse events depends on several factors: the dose of the drug and duration of treatment; the age, the sex, physical condition of the patient; any concurrent medical diagnoses or individual risk factors. The following adverse reactions are divided into three parts based on frequency and whether or not the possibility exists of a causal relationship between drug usage and these adverse events. In those reactions listed as “Probable Causal Relationship” there is at least one case for each adverse reaction where there is evidence to suggest that there is a causal relationship between drug usage and the reported event. The adverse reactions reported were based on the results from two double-blind controlled clinical trials of three months duration with an additional nine month open-label extension. A total of 542 patients received NAPRELAN Tablets either in the double-blind period or in the nine month open-label extension. Of these 542 patients, 232 received NAPRELAN Tablets, 167 were initially treated with Naprosyn® and 143 were initially treated with placebo. Adverse reactions reported by patients who received NAPRELAN Tablets are shown by body system. Those adverse reactions observed with naproxen but not reported in controlled trials with NAPRELAN Tablets are italicized.

The most frequent adverse events from the double-blind and open-label clinical trials were headache (15%), followed by dyspepsia (14%), and flu syndrome (10%). The incidence of other adverse events occurring in 3% to 9% of the patients are marked with an asterisk.

Those reactions occurring in less than 3% of the patients are unmarked.

Incidence greater than 1% (probable causal relationship)

Body as a Whole—Pain (back)*, pain*, infection*, fever, injury (accident), asthenia, pain chest, headache (15%), flu syndrome (10%).

Gastrointestinal—Nausea*, diarrhea*, constipation*, abdominal pain*, flatulence, gastritis, vomiting, dysphagia, dyspepsia (14%), heartburn*, stomatitis.

Hematologic—Anemia, ecchymosis.

Respiratory—Pharyngitis*, rhinitis*, sinusitis*, bronchitis, cough increased.

Renal—Urinary tract infection*, cystitis.

Dermatologic—Skin rash*, skin eruptions*, ecchymoses*, purpura.

Metabolic and Nutrition—Peripheral edema, hyperglycemia.

Central Nervous System—Dizziness, paresthesia, insomnia, drowsiness*, lightheadedness.

Cardiovascular—Hypertension, edema*, dyspnea*, palpitations.

Musculoskeletal—Cramps (leg), myalgia, arthralgia, joint disorder, tendon disorder.

Special Senses—Tinnitus*, hearing disturbances, visual disturbances.

General—Thirst.

Incidence less than 1% (probable causal relationship)
Body as a Whole—Abscess, monilia, neck rigid, pain neck, abdomen enlarged, carcinoma, cellulitis, edema general, LE syndrome, malaise, mucous membrane disorder, allergic reaction, pain pelvic.

Gastrointestinal—Anorexia, cholecystitis, cholelithiasis, eructation, GI hemorrhage, rectal hemorrhage, stomatitis aphthous, stomatitis ulcer, ulcer mouth, ulcer stomach, periodontal abscess, cardiospasm, colitis, esophagitis, gastroenteritis, GI disorder, rectal disorder, tooth disorder, hepatosplenomegaly, liver function abnormality, melena, ulcer esophagus, hematemesis, jaundice, pancreatitis, necrosis.

Renal—Dysmenorrhea, dysuria, kidney function abnormality, nocturia, prostate disorder, pyelonephritis, carcinoma breast, urinary incontinence, kidney calculus, kidney failure, menorrhagia, metrorrhagia, neoplasm breast, nephrosclerosis, hematuria, pain kidney, pyuria, urine abnormal, urinary frequency, urinary retention, uterine spasm, vaginitis, glomerular nephritis, hyperkalemia, interstitial nephritis, nephrotic syndrome, renal disease, renal failure, renal papillary necrosis.

Hematologic—Leukopenia, bleeding time increased, eosinophilia, abnormal RBC, abnormal WBC, thrombocytopenia, agranulocytosis, granulocytopenia.

Central Nervous System—Depression, anxiety, hypertonia, nervousness, neuralgia, neuritis, vertigo, amnesia, confusion, co-ordination, abnormal diplopia, emotional lability, hematoma subdural, paralysis, dream abnormalities, inability to concentrate, muscle weakness.

Dermatologic: Angiodermatitis, herpes simplex, dry skin, sweating, ulcer skin, acne, alopecia, dermatitis contact, eczema, herpes zoster, nail disorder, skin necrosis, subcutaneous nodule, pruritus, urticaria, neoplasm skin, photosensitive dermatitis, photosensitivity reactions resembling porphyria cutaneous tarda, epidermolysis bullosa.

Special Senses—Amblyopia, scleritis, cataract, conjunctivitis, deaf, ear disorder, keratoconjunctivitis, lacrimation disorder, otitis media, pain eye.

Cardiovascular—Angina pectoris, coronary artery disease, myocardial infarction, deep thrombophlebitis, vasodilation, vascular anomaly, arrhythmia, bundle branch block, abnormal ECG, heart failure right, hemorrhage, migraine, aortic stenosis, syncope, tachycardia, congestive heart failure.

Respiratory—Asthma, dyspnea, lung edema, laryngitis, lung disorder, epistaxis, pneumonia, respiratory distress, respiratory disorder, eosinophilic pneumonitis.

Musculoskeletal—Myasthenia, bone disorder, spontaneous bone fracture, fibrotendinitis, bone pain, ptosis, spasm general, bursitis.

Metabolic and Nutrition—Creatinine increase, glucosuria, hypercholesteremia, albuminuria, alkalosis, BUN increased, dehydration, edema, glucose tolerance decrease, hyperuricemia, hypokalemia, SGOT increase, SGPT increase, weight decrease.

General—Anaphylactoid reactions, angioneurotic edema, menstrual disorders, hypoglycemia, pyrexia (chills and fevers).

Incidence less than 1% (causal relationship unknown)
Other adverse reactions listed in the naproxen package label, but not reported by those who received NAPRELAN Tablets are shown in italics. These observations are being listed as alerting information to the physician.

Hematologic—Aplastic anemia, hemolytic anemia.

Central Nervous System—Aseptic meningitis, cognitive dysfunction.

Dermatologic—Epidermal necrolysis, erythema multiforme, Stevens-Johnson syndrome.

Gastrointestinal—Non-peptic GI ulceration, ulcerative stomatitis.

Cardiovascular—Vasculitis.

6.2 Postmarketing Experience

The following adverse reactions have been identified during postapproval use of naproxen. Because these reactions are reported voluntarily from a population of uncertain size, it is not always possible to reliably estimate their frequency or establish a causal relationship to drug exposure.
Skin and Appendages: Exfoliative dermatitis, Stevens-Johnson Syndrome (SJS), toxic epidermal necrolysis (TEN), and fixed drug eruption (FDE).

7 DRUG INTERACTIONS

See Table 1 for clinically significant drug interactions with naproxen.

Table 1: Clinically Significant Drug Interactions with Naproxen

Drugs That Interfere with Hemostasis
Clinical Impact: | - Naproxen and anticoagulants such as warfarin have a synergistic effect on bleeding. The concomitant use of naproxen and anticoagulants have an increased risk of serious bleeding compared to the use of either drug alone. - Serotonin release by platelets plays an important role in hemostasis. Case-control and cohort epidemiological studies showed that concomitant use of drugs that interfere with serotonin reuptake and an NSAID may potentiate the risk of bleeding more than an NSAID alone.
Intervention: | Monitor patients with concomitant use of NAPRELAN with anticoagulants (e.g., warfarin), antiplatelet agents (e.g., aspirin), selective serotonin reuptake inhibitors (SSRIs), and serotonin norepinephrine reuptake inhibitors (SNRIs) for signs of bleeding [see Warnings and Precautions (5.12)].
Aspirin
Clinical Impact: | A pharmacodynamic (PD) study has demonstrated an interaction in which lower dose naproxen (220 mg/day or 220 mg twice daily) interfered with the antiplatelet effect of low-dose immediate-release aspirin, with the interaction most marked during the washout period of naproxen [see Clinical Pharmacology (12.2)]. There is reason to expect that the interaction would be present with prescription doses of naproxen or with enteric-coated low-dose aspirin; however, the peak interference with aspirin function may be later than observed in the PD study due to the longer washout period. Controlled clinical studies showed that the concomitant use of NSAIDs and analgesic doses of aspirin does not produce any greater therapeutic effect than the use of NSAIDs alone. In a clinical study, the concomitant use of an NSAID and aspirin was associated with a significantly increased incidence of GI adverse reactions as compared to use of the NSAID alone [see Warnings and Precautions (5.2)].
Intervention: | Because there may be an increased risk of cardiovascular events following discontinuation of naproxen due to the interference with the antiplatelet effect of aspirin during the washout period, for patients taking low-dose aspirin for cardio protection who require intermittent analgesics, consider use of an NSAID that does not interfere with the antiplatelet effect of aspirin, or non-NSAID analgesics where appropriate. Concomitant use of NAPRELAN and analgesic doses of aspirin is not generally recommended because of the increased risk of bleeding [see Warnings and Precautions (5.12)]. NAPRELAN is not a substitute for low dose aspirin for cardiovascular protection.
ACE Inhibitors, Angiotensin Receptor Blockers, and Beta-Blockers
Clinical Impact: | - NSAIDs may diminish the antihypertensive effect of angiotensin converting enzyme (ACE) inhibitors, angiotensin receptor blockers (ARBs), or beta-blockers (including propranolol). - In patients who are elderly, volume-depleted (including those on diuretic therapy), or have renal impairment, co-administration of an NSAID with ACE inhibitors or ARBs may result in deterioration of renal function, including possible acute renal failure. These effects are usually reversible.
Intervention: | - During concomitant use of NAPRELAN and ACE-inhibitors, ARBs, or beta-blockers, monitor blood pressure to ensure that the desired blood pressure is obtained. - During concomitant use of NAPRELAN and ACE-inhibitors or ARBs in patients who are elderly, volume-depleted, or have impaired renal function, monitor for signs of worsening renal function [see Warnings and Precautions (5.6)]. - When these drugs are administered concomitantly, patients should be adequately hydrated. Assess renal function at the beginning of the concomitant treatment and periodically thereafter.
Diuretics
Clinical Impact: | Clinical studies, as well as post-marketing observations, showed that NSAIDs reduced the natriuretic effect of loop diuretics (e.g., furosemide) and thiazide diuretics in some patients. This effect has been attributed to the NSAID inhibition of renal prostaglandin synthesis.
Intervention: | During concomitant use of NAPRELAN with diuretics, observe patients for signs of worsening renal function, in addition to assuring diuretic efficacy including antihypertensive effects [see Warnings and Precautions (5.6)].
Digoxin
Clinical Impact: | The concomitant use of naproxen with digoxin has been reported to increase the serum concentration and prolong the half-life of digoxin.
Intervention: | During concomitant use of NAPRELAN and digoxin, monitor serum digoxin levels.
Lithium
Clinical Impact: | NSAIDs have produced elevations in plasma lithium levels and reductions in renal lithium clearance. The mean minimum lithium concentration increased 15%, and the renal clearance decreased by approximately 20%. This effect has been attributed to NSAID inhibition of renal prostaglandin synthesis.
Intervention: | During concomitant use of NAPRELAN and lithium, monitor patients for signs of lithium toxicity.
Methotrexate
Clinical Impact: | Concomitant use of NSAIDs and methotrexate may increase the risk for methotrexate toxicity (e.g., neutropenia, thrombocytopenia, renal dysfunction).
Intervention: | During concomitant use of NAPRELAN and methotrexate, monitor patients for methotrexate toxicity.
Cyclosporine
Clinical Impact: | Concomitant use of NAPRELAN and cyclosporine may increase cyclosporine’s nephrotoxicity.
Intervention: | During concomitant use of NAPRELAN and cyclosporine, monitor patients for signs of worsening renal function.
NSAIDs and Salicylates
Clinical Impact: | Concomitant use of naproxen with other NSAIDs or salicylates (e.g., diflunisal, salsalate) increases the risk of GI toxicity, with little or no increase in efficacy [see Warnings and Precautions (5.2)].
Intervention: | The concomitant use of naproxen with other NSAIDs or salicylates is not recommended.
Pemetrexed
Clinical Impact: | Concomitant use of NAPRELAN and pemetrexed may increase the risk of pemetrexed-associated myelosuppression, renal, and GI toxicity (see the pemetrexed prescribing information).
Intervention: | During concomitant use of NAPRELAN and pemetrexed, in patients with renal impairment whose creatinine clearance ranges from 45 to 79 mL/min, monitor for myelosuppression, renal and GI toxicity.; NSAIDs with short elimination half-lives (e.g., diclofenac, indomethacin) should be avoided for a period of two days before, the day of, and two days following administration of pemetrexed.; In the absence of data regarding potential interaction between pemetrexed and NSAIDs with longer half-lives (e.g., meloxicam, nabumetone), patients taking these NSAIDs should interrupt dosing for at least five days before, the day of, and two days following pemetrexed administration.
Antacids and Sucralfate
Clinical Impact: | Concomitant administration of some antacids (magnesium oxide or aluminum hydroxide) and sucralfate can delay the absorption of naproxen.
Intervention: | Concomitant administration of antacids such as magnesium oxide or aluminum hydroxide, and sucralfate with NAPRELAN is not recommended.
Cholestyramine
Clinical Impact: | Concomitant administration of cholestyramine can delay the absorption of naproxen.
Intervention: | Concomitant administration of cholestyramine with NAPRELAN is not recommended.
Probenecid
Clinical Impact: | Probenecid given concurrently increases naproxen anion plasma levels and extends its plasma half-life significantly.
Intervention: | Patients simultaneously receiving NAPRELAN and probenecid should be observed for adjustment of dose if required.
Other albumin-bound drugs
Clinical Impact: | Naproxen is highly bound to plasma albumin; it thus has a theoretical potential for interaction with other albumin-bound drugs such as coumarin-type anticoagulants, sulphonylureas, hydantoins, other NSAIDs, and aspirin.
Intervention: | Patients simultaneously receiving NAPRELAN and a hydantoin, sulphonamide or sulphonylurea should be observed for adjustment of dose if required.

Drug/Laboratory Test Interactions

Bleeding times
Clinical Impact: | Naproxen may decrease platelet aggregation and prolong bleeding time.
Intervention: | This effect should be kept in mind when bleeding times are determined.
Porter-Silber test
Clinical Impact: | The administration of naproxen may result in increased urinary values for 17-ketogenic steroids because of an interaction between the drug and/or its metabolites with m-di-nitrobenzene used in this assay.
Intervention: | Although 17-hydroxy-corticosteroid measurements (Porter-Silber test) do not appear to be artifactually altered, it is suggested that therapy with NAPRELAN be temporarily discontinued 72 hours before adrenal function tests are performed if the Porter-Silber test is to be used.
Urinary assays of 5-hydroxy indoleacetic acid (5HIAA)
Clinical Impact: | Naproxen may interfere with some urinary assays of 5-hydroxy indoleacetic acid (5HIAA).
Intervention: | This effect should be kept in mind when urinary 5-hydroxy indoleacetic acid are determined.

8 USE IN SPECIFIC POPULATIONS

8.1 Pregnancy

Risk Summary

Use of NSAIDs, including NAPRELAN, can cause premature closure of the fetal ductus arteriosus and fetal renal dysfunction leading to oligohydramnios and, in some cases, neonatal renal impairment. Because of these risks, limit dose and duration of NAPRELAN use between about 20 and 30 weeks of gestation, and avoid NAPRELAN use at about 30 weeks of gestation and later in pregnancy (see Clinical Considerations, Data).

Premature Closure of Fetal Ductus Arteriosus

Use of NSAIDs, including NAPRELAN, at about 30 weeks gestation or later in pregnancy increases the risk of premature closure of the fetal ductus arteriosus.

Oligohydramnios/Neonatal Renal Impairment

Use of NSAIDs at about 20 weeks gestation or later in pregnancy has been associated with cases of fetal renal dysfunction leading to oligohydramnios, and in some cases, neonatal renal impairment.

Data from observational studies regarding other potential embryofetal risks of NSAID use in women in the first or second trimesters of pregnancy are inconclusive. In animal reproduction studies in rats, rabbit, and mice no evidence of teratogenicity or fetal harm when naproxen was administered during the period of organogenesis at doses 0.13, 0.26, and 0.6 times the maximum recommended human daily dose of 1,500 mg/day, respectively. Based on animal data, prostaglandins have been shown to have an important role in endometrial vascular permeability, blastocyst implantation, and decidualization. In animal studies, administration of prostaglandin synthesis inhibitors such as naproxen, resulted in increased pre and post-implantation loss. Prostaglandins also have been shown to have an important role in fetal kidney development. In published animal studies, prostaglandin synthesis inhibitors have been reported to impair kidney development when administered at clinically relevant doses.

The estimated background risk of major birth defects and miscarriage for the indicated population(s) is unknown. All pregnancies have a background risk of birth defect, loss, or other adverse outcomes. In the U.S. general population, the estimated background risk of major birth defects and miscarriage in clinically recognized pregnancies is 2% to 4% and 15% to 20%, respectively.

Clinical Considerations

Fetal/Neonatal Adverse Reactions

Premature Closure of Fetal Ductus Arteriosus

Avoid use of NSAIDs in women at about 30 weeks gestation and later in pregnancy, because NSAIDs, including NAPRELAN, can cause premature closure of the fetal ductus arteriosus (see Data).

Oligohydramnios/Neonatal Renal Impairment

If an NSAID is necessary at about 20 weeks gestation or later in pregnancy, limit the use to the lowest effective dose and shortest duration possible. If NAPRELAN treatment extends beyond 48 hours, consider monitoring with ultrasound for oligohydramnios. If oligohydramnios occurs, discontinue NAPRELAN and follow up according to clinical practice (see Data).

Labor or Delivery
There are no studies on the effects of NAPRELAN during labor or delivery. In animal studies, NSAIDS, including naproxen sodium, inhibit prostaglandin synthesis, cause delayed parturition, increase incidence of dystocia and increase the incidence of stillbirth.

Data
Human Data
There is some evidence to suggest that when inhibitors of prostaglandin synthesis are used to delay preterm labor, there is an increased risk of neonatal complications such as necrotizing enterocolitis, patent ductus arteriosus, and intracranial hemorrhage. Naproxen treatment given in late pregnancy to delay parturition has been associated with persistent pulmonary hypertension, renal dysfunction, and abnormal prostaglandin E levels in preterm infants. Because of the known effect of drugs of this class on the human fetal cardiovascular system (closure of the ductus arteriosus), use during third trimester should be avoided.

Premature Closure of Fetal Ductus Arteriosus:

Published literature reports that the use of NSAIDs at about 30 weeks of gestation and later in pregnancy may cause premature closure of the fetal ductus arteriosus.

Oligohydramnios/Neonatal Renal Impairment:

Published studies and postmarketing reports describe maternal NSAID use at about 20 weeks gestation or later in pregnancy associated with fetal renal dysfunction leading to oligohydramnios, and in some cases, neonatal renal impairment. These adverse outcomes are seen, on average, after days to weeks of treatment, although oligohydramnios has been infrequently reported as soon as 48 hours after NSAID initiation. In many cases, but not all, the decrease in amniotic fluid was transient and reversible with cessation of the drug. There have been a limited number of case reports of maternal NSAID use and neonatal renal dysfunction without oligohydramnios, some of which were irreversible. Some cases of neonatal renal dysfunction required treatment with invasive procedures, such as exchange transfusion or dialysis.

Methodological limitations of these postmarketing studies and reports include lack of a control group; limited information regarding dose, duration, and timing of drug exposure; and concomitant use of other medications. These limitations preclude establishing a reliable estimate of the risk of adverse fetal and neonatal outcomes with maternal NSAID use. Because the published safety data on neonatal outcomes involved mostly preterm infants, the generalizability of certain reported risks to the full-term infant exposed to NSAIDs through maternal use is uncertain.

Animal data
Reproduction studies have been performed in rats at 20 mg/kg/day (0.13 times the maximum recommended human daily dose of 1,500 mg/day based on body surface area comparison) rabbits at 20 mg/kg/day (0.26 times the maximum recommended human daily dose, based on body surface area comparison), and mice at 170 mg/kg/day (0.6 times the maximum recommended human daily dose based on body surface area comparison) with no evidence of impaired fertility or harm to the fetus due to the drug. Based on animal data, prostaglandins have been shown to have an important role in endometrial vascular permeability, blastocyst implantation, and decidualization. In animal studies, administration of prostaglandin synthesis inhibitors such as naproxen sodium resulted in increased pre- and post-implantation loss.

8.2 Lactation

Risk Summary
The naproxen anion has been found in the milk of lactating women at a concentration of approximately 1% of that found in the plasma. The developmental and health benefits of breastfeeding should be considered along with the mother’s clinical need for NAPRELAN and any potential adverse effects on the breastfed infant from the NAPRELAN or from the underlying maternal condition.

8.3 Females and Males of Reproductive Potential

Infertility
Females
Based on the mechanism of action, the use of prostaglandin-mediated NSAIDs, including NAPRELAN, may delay or prevent rupture of ovarian follicles, which has been associated with reversible infertility in some women. Published animal studies have shown that administration of prostaglandin synthesis inhibitors has the potential to disrupt prostaglandin-mediated follicular rupture required for ovulation. Small studies in women treated with NSAIDs have also shown a reversible delay in ovulation. Consider withdrawal of NSAIDs, including NAPRELAN, in women who have difficulties conceiving or who are undergoing investigation of infertility.

8.4 Pediatric Use

The safety and effectiveness of NAPRELAN in pediatric populations has not been established.

8.5 Geriatric Use

Elderly patients, compared to younger patients, are at greater risk for NSAID-associated serious cardiovascular, gastrointestinal, and/or renal adverse reactions. If the anticipated benefit for the elderly patient outweighs these potential risks, start dosing at the low end of the dosing range, and monitor patients for adverse effects [see Warnings and Precautions (5.1,5.2,5.3,5.6, 5.14)].

Naproxen and its metabolites are known to be substantially excreted by the kidney, and the risk of adverse reactions to this drug may be greater in patients with impaired renal function. Because elderly patients are more likely to have decreased renal function, use caution in this patient population, and it may be useful to monitor renal function [see Clinical Pharmacology (12.3)].

10 OVERDOSAGE

Symptoms following acute NSAID overdosages have been typically limited to lethargy, drowsiness, nausea, vomiting, and epigastric pain, which have been generally reversible with supportive care. Gastrointestinal bleeding has occurred. Hypertension, acute renal failure, respiratory depression, and coma have occurred, but were rare [see Warnings and Precautions (5.1, 5.2, 5.4, 5.6)].

A few patients have experienced seizures, but it is not clear whether or not these were drug-related. It is not known what dose of the drug would be life threatening.

Manage patients with symptomatic and supportive care following an NSAID overdosage. There are no specific antidotes. Hemodialysis does not decrease the plasma concentration of naproxen because of the high degree of its protein binding. Consider emesis and/or activated charcoal (60 to 100 grams in adults, 1 to 2 grams per kg of body weight in pediatric patients) and/or osmotic cathartic in symptomatic patients seen within four hours of ingestion or in patients with a large overdosage (5 to 10 times the recommended dosage). Forced diuresis, alkalinization of urine, hemodialysis, or hemoperfusion may not be useful due to high protein binding.

For additional information about overdosage treatment contact a poison control center (1-800-222-1222).

11 DESCRIPTION

NAPRELAN (naproxen sodium) Controlled-Release Tablets is a nonsteroidal anti-inflammatory drug, available as controlled-release tablets in 375 mg, 500 mg, and 750 mg strengths for oral administration. The chemical name is 2-naphthaleneacetic acid, 6-methoxy-α-methyl-sodium salt, (S)-. The molecular weight is 252.24. Its molecular formula is C14H13NaO3, and it has the following chemical structure.

Naproxen sodium is an odorless crystalline powder, white to creamy in color. It is soluble in methanol and water. NAPRELAN Tablets contain 412.5 mg, 550 mg, or 825 mg of naproxen sodium, equivalent to 375 mg, 500 mg, and 750 mg of naproxen, and 37.5 mg, 50 mg, and 75 mg sodium respectively. Each NAPRELAN Tablet also contains the following inactive ingredients: ammoniomethacrylate copolymer Type A, ammoniomethacrylate copolymer Type B, citric acid, crospovidone, magnesium stearate, methacrylic acid copolymer Type A, microcrystalline cellulose, povidone, and talc. The tablet coating contains hydroxypropyl methylcellulose, polyethylene glycol, and titanium dioxide.

12 CLINICAL PHARMACOLOGY

12.1 Mechanism of Action

Naproxen has analgesic, anti-inflammatory, and antipyretic properties.

The mechanism of action of NAPRELAN, like that of other NSAIDs, is not completely understood but involves inhibition of cyclooxygenase (COX-1 and COX-2).

Naproxen sodium is a potent inhibitor of prostaglandin synthesis in vitro. Naproxen sodium concentrations reached during therapy have produced in vivo effects. Prostaglandins sensitize afferent nerves and potentiate the action of bradykinin in inducing pain in animal models. Prostaglandins are mediators of inflammation. Because naproxen sodium is an inhibitor of prostaglandin synthesis, its mode of action may be due to a decrease of prostaglandins in peripheral tissues.

12.2 Pharmacodynamics

In a healthy volunteer study, 10 days of concomitant administration of naproxen 220 mg once-daily with low-dose immediate-release aspirin (81 mg) showed an interaction with the antiplatelet activity of aspirin as measured by % serum thromboxane B2 inhibition at 24 hours following the day 10 dose [98.7% (aspirin alone) vs 93.1% (naproxen and aspirin)]. The interaction was observed even following discontinuation of naproxen on day 11 (while aspirin dose was continued) but normalized by day 13. In the same study, the interaction was greater when naproxen was administered 30 minutes prior to aspirin [98.7% vs 87.7%] and minimal when aspirin was administered 30 minutes prior to naproxen [98.7% vs 95.4%].
Following administration of naproxen 220 mg twice-daily with low-dose immediate-release aspirin (first naproxen dose given 30 minutes prior to aspirin), the interaction was minimal at 24 h following day 10 dose [98.7% vs 95.7%]. However, the interaction was more prominent after discontinuation of naproxen (washout) on day 11 [98.7% vs 84.3%] and did not normalize completely by day 13 [98.5% vs 90.7%]. [see Drug Interactions (7)].

12.3 Pharmacokinetics

Although naproxen itself is well absorbed, the sodium salt form is more rapidly absorbed, resulting in higher peak plasma levels for a given dose. Approximately 30% of the total naproxen sodium dose in NAPRELAN Tablets is present in the dosage form as an immediate release component. The remaining naproxen sodium is coated as microparticles to provide sustained release properties. After oral administration, plasma levels of naproxen are detected within 30 minutes of dosing, with peak plasma levels occurring approximately 5 hours after dosing. The observed terminal elimination half-life of naproxen from both immediate release naproxen sodium and NAPRELAN Tablets is approximately 15 hours. Steady state levels of naproxen are achieved in 3 days and the degree of naproxen accumulation in the blood is consistent with this.

Pharmacokinetic Parameters at Steady State Day 5 (Mean of 24 Subjects)

Parameter (units) | naproxen 500 mg Q12h/5 days (1000 mg) |  |  | NAPRELAN 2 x 500 mg tablets (1000 mg) Q24h/5 days
 | Mean | SD | Range | Mean | SD | Range
AUC 0-24 (mcgxh/mL) | 1446 | 168 | 1167 - 1858 | 1448 | 145 | 1173 - 1774
Cmax(mcg/mL) | 95 | 13 | 71 - 117 | 94 | 13 | 74 - 127
Cavg (mcg/mL) | 60 | 7 | 49 - 77 | 60 | 6 | 49 - 74
Cmin (mcg/mL) | 36 | 9 | 13 - 51 | 33 | 7 | 23 - 48
Tmax (hrs) | 3 | 1 | 1 - 4 | 5 | 2 | 2-10

Absorption
Naproxen itself is rapidly and completely absorbed from the GI tract with an in vivo bioavailability of 95%. Based on the pharmacokinetic profile, the absorption phase of NAPRELAN Tablets occurs in the first 4 to 6 hours after administration. This coincides with disintegration of the tablet in the stomach, the transit of the sustained release microparticles through the small intestine and into the proximal large intestine. An in vivo imaging study has been performed in healthy volunteers that confirms rapid disintegration of the tablet matrix and dispersion of the microparticles.

The absorption rate from the sustained release particulate component of NAPRELAN Tablets is slower than that for conventional naproxen sodium tablets. It is this prolongation of drug absorption processes that maintains plasma levels and allows for once daily dosing.

Food Effects
No significant food effects were observed when twenty-four subjects were given a single dose of NAPRELAN Tablets 500 mg either after an overnight fast or 30 minutes after a meal. In common with conventional naproxen and naproxen sodium formulations, food causes a slight decrease in the rate of naproxen absorption following NAPRELAN Tablets administration.

Distribution
Naproxen has a volume of distribution of 0.16 L/kg. At therapeutic levels, naproxen is greater than 99% albumin-bound. At doses of naproxen greater than 500 mg/day, there is a less than proportional increase in plasma levels due to an increase in clearance caused by saturation of plasma protein binding at higher doses. However the concentration of unbound naproxen continues to increase proportionally to dose. NAPRELAN Tablets exhibit similar dose proportional characteristics.

Elimination
Metabolism
Naproxen is extensively metabolized to 6-0-desmethyl naproxen and both parent and metabolites do not induce metabolizing enzymes.

Excretion
The elimination half-life of NAPRELAN Tablets and conventional naproxen is approximately 15 hours. Steady state conditions are attained after 2 to 3 doses of NAPRELAN Tablets. Most of the drug is excreted in the urine, primarily as unchanged naproxen (less than 1%), 6-0-desmethyl naproxen (less than 1%) and their glucuronide or other conjugates (66 to 92%). A small amount (<5%) of the drug is excreted in the feces. The rate of excretion has been found to coincide closely with the rate of clearance from the plasma. In patients with renal failure, metabolites may accumulate.

Specific Populations
Pediatric:
No pediatric studies have been performed with NAPRELAN Tablets, thus safety of NAPRELAN Tablets in pediatric populations has not been established.

Hepatic Impairment:
Chronic alcoholic liver disease and probably other diseases with decreased or abnormal plasma proteins (albumin) reduce the total plasma concentration of naproxen, but the plasma concentration of unbound naproxen is increased. Caution is advised when high doses are required and some adjustment of dosage may be required in these patients. It is prudent to use the lowest effective dose.

Renal Impairment:
Naproxen pharmacokinetics have not been determined in subjects with renal insufficiency. Given that naproxen is metabolized and conjugates are primarily excreted by the kidneys, the potential exists for naproxen metabolites to accumulate in the presence of renal insufficiency. Elimination of naproxen is decreased in patients with severe renal impairment. Naproxen-containing products are not recommended for use in patients with moderate to severe and severe renal impairment (creatinine clearance <30mL/min) [see Warnings and Precautions (5.6)].

Drug Interaction Studies
Aspirin: When NSAIDs were administered with aspirin, the protein binding of NSAIDs were reduced, although the clearance of free NSAID was not altered. The clinical significance of this interaction is not known. See Table 1 for clinically significant drug interactions of NSAIDs with aspirin [see Drug Interactions (7)].

13 NONCLINICAL TOXICOLOGY

13.1 Carcinogenesis, Mutagenesis, Impairment of Fertility

Carcinogenesis
A two year study was performed in rats to evaluate the carcinogenic potential of naproxen at doses of 8 mg/kg/day, 16 mg/kg/day, and 24 mg/kg/day (0.05, 0.1, and 0.16 times the maximum recommended human daily dose of 1,500 mg/day based on a body surface area comparison). No evidence of tumorigenicity was found.

Mutagenesis
Studies to evaluate the mutagenic potential of Naprosyn Suspension have not been completed.

Impairment of Fertility
Studies to evaluate the impact of naproxen on male or female fertility have not been completed.

14 CLINICAL STUDIES

Rheumatoid Arthritis
The use of NAPRELAN Tablets for the management of the signs and symptoms of rheumatoid arthritis was assessed in a 12 week double-blind, randomized, placebo, and active-controlled study in 348 patients. Two NAPRELAN 500 mg tablets (1,000 mg) once daily and naproxen 500 mg tablets twice daily (1,000 mg) were more effective than placebo. Clinical effectiveness was demonstrated at one week and continued for the duration of the study.

Osteoarthritis
The use of NAPRELAN Tablets for the management of the signs and symptoms of osteoarthritis of the knee was assessed in a 12 week double-blind, placebo, and active-controlled study in 347 patients. Two NAPRELAN 500 mg tablets (1,000 mg) once daily and naproxen 500 mg tablets twice daily (1,000 mg) were more effective than placebo. Clinical effectiveness was demonstrated at one week and continued for the duration of the study.

Analgesia
The onset of the analgesic effect of NAPRELAN Tablets was seen within 30 minutes in a pharmacokinetic/pharmacodynamic study of patients with pain following oral surgery. In controlled clinical trials, naproxen has been used in combination with gold, D-penicillamine, methotrexate, and corticosteroids. Its use in combination with salicylate is not recommended because there is evidence that aspirin increases the rate of excretion of naproxen and data are inadequate to demonstrate that naproxen and aspirin produce greater improvement over that achieved with aspirin alone. In addition, as with other NSAIDs the combination may result in higher frequency of adverse events than demonstrated for either product alone.

Special Studies
In a double-blind randomized, parallel group study, 19 subjects received either two NAPRELAN 500 mg tablets (1,000 mg) once daily or naproxen 500 mg tablets (1,000 mg) twice daily for 7 days. Mucosal biopsy scores and endoscopic scores were lower in the subjects who received NAPRELAN Tablets. In another double-blind, randomized, crossover study, 23 subjects received two NAPRELAN 500 mg tablets (1,000 mg) once daily, naproxen 500 mg tablets (1,000 mg) twice daily and aspirin 650 mg four times daily (2,600 mg) for 7 days each. There were significantly fewer duodenal erosions seen with NAPRELAN Tablets than with either naproxen or aspirin. There were significantly fewer gastric erosions with both NAPRELAN Tablets and naproxen than with aspirin. The clinical significance of these findings is unknown.

16 HOW SUPPLIED/STORAGE AND HANDLING

NAPRELAN (naproxen sodium) 375 mg, 500 mg, and 750 mg are controlled-release tablets supplied as:

NAPRELAN 375: white, capsule-shaped tablet with “N” on one side and “375” on the reverse; in bottles of 100; NDC 24979-249-01. Each tablet contains 412.5 mg naproxen sodium equivalent to 375 mg naproxen.

NAPRELAN 500: white, capsule-shaped tablet with “N” on one side and “500” on the reverse; in bottles of 75; NDC 24979-250-68. Each tablet contains 550 mg naproxen sodium equivalent to 500 mg naproxen.

NAPRELAN 750: white, capsule-shaped tablet with “N” on one side and “750” on the reverse; in bottles of 30; NDC 24979-251-06. Each tablet contains 825 mg naproxen sodium equivalent to 750 mg naproxen.

Storage

Store at room temperature, 20°C to 25°C (68°F to 77°F), excursions permitted 15°C to 30°C (59°F to 86°F) [see USP Controlled Room Temperature]. PHARMACIST: Dispense in a well-closed container.

17 PATIENT COUNSELING INFORMATION

Advise the patient to read the FDA-approved patient labeling (Medication Guide) that accompanies each prescription dispensed. Inform patients, families, or their caregivers of the following information before initiating therapy with NAPRELAN and periodically during the course of ongoing therapy.

Cardiovascular Thrombotic Events
Advise patients to be alert for the symptoms of cardiovascular thrombotic events, including chest pain, shortness of breath, weakness, or slurring of speech, and to report any of these symptoms to their health care provider immediately [see Warnings and Precautions (5.1)].

Gastrointestinal Bleeding, Ulceration, and Perforation
NAPRELAN, like other NSAIDs, can cause GI discomfort and, rarely, serious GI side effects, such as ulcers and bleeding, which may result in hospitalization and even death. Advise patients to report symptoms of ulcerations and bleeding, including epigastric pain, dyspepsia, melena, and hematemesis to their health care provider. In the setting of concomitant use of low-dose aspirin for cardiac prophylaxis, inform patients of the increased risk for and the signs and symptoms of GI bleeding [see Warnings and Precautions (5.2)].

Hepatotoxicity
Inform patients of the warning signs and symptoms of hepatotoxicity (e.g., nausea, fatigue, lethargy, pruritus, diarrhea, jaundice, right upper quadrant tenderness, and “flu-like” symptoms). If these occur, instruct patients to stop NAPRELAN and seek immediate medical therapy [see Warnings and Precautions (5.3)].

Heart Failure and Edema
Advise patients to be alert for the symptoms of congestive heart failure including shortness of breath, unexplained weight gain, or edema and to contact their healthcare provider if such symptoms occur [see Warnings and Precautions (5.5)].

Anaphylactic Reactions
Inform patients of the signs of an anaphylactic reaction (e.g., difficulty breathing, swelling of the face or throat). Instruct patients to seek immediate emergency help if these occur [see Contraindications (4) and Warnings and Precautions (5.7)].

Serious Skin Reactions, including DRESS
NAPRELAN, like other NSAIDs, can cause serious skin side effects such as exfoliative dermatitis, SJS, and TEN, which may result in hospitalization and even death. Advise patients to stop taking NAPRELAN immediately if they develop any type of rash or fever and to contact their healthcare provider as soon as possible [see Warnings and Precautions (5.9, 5.10)].

Female Fertility
Advise females of reproductive potential who desire pregnancy that NSAIDs, including NAPRELAN, may be associated with a reversible delay in ovulation [see Use in Specific Populations (8.3)].

Fetal Toxicity
Inform pregnant women to avoid use of NAPRELAN and other NSAIDs starting at 30 weeks gestation because of the risk of the premature closing of the fetal ductus arteriosus. If treatment with NAPRELAN is needed for a pregnant woman between about 20 to 30 weeks gestation, advise her that she may need to be monitored for oligohydramnios, if treatment continues for longer than 48 hours [see Warnings and Precautions (5.11) and Use in Specific Populations (8.1)].

Avoid Concomitant Use of NSAIDs
Inform patients that the concomitant use of NAPRELAN with other NSAIDs or salicylates (e.g., diflunisal, salsalate) is not recommended due to the increased risk of gastrointestinal toxicity, and little or no increase in efficacy [see Warnings and Precautions (5.2) and Drug Interactions (7)]. Alert patients that NSAIDs may be present in “over the counter” medications for treatment of colds, fever, or insomnia.

Use of NSAIDS and Low-Dose Aspirin
Inform patients not to use low-dose aspirin concomitantly with NAPRELAN until they talk to their healthcare provider [see Drug Interactions (7)].

All trademarks are the property of their respective owners.

Distributed by:
TWi Pharmaceuticals USA, Inc.
Paramus, NJ 07652

PKG03116

Rev. 11/2024

Medication Guide for Nonsteroidal Anti-inflammatory Drugs (NSAIDs)

What is the most important information I should know about medicines called Nonsteroidal Anti-inflammatory Drugs (NSAIDs)?
NSAIDs can cause serious side effects, including:

- Increased risk of a heart attack or stroke that can lead to death.This risk may happen early in treatment and may increase:
  - with increasing doses of NSAIDs
  - with longer use of NSAIDs
  Do not take NSAIDs right before or after a heart surgery called a "coronary artery bypass graft (CABG)."
  Avoid taking NSAIDs after a recent heart attack, unless your healthcare provider tells you to. You may have an increased risk of another heart attack if you take NSAIDs after a recent heart attack.
- Increased risk of bleeding, ulcers, and tears (perforation) of the esophagus (tube leading from the mouth to the stomach), stomach and intestines:
  - anytime during use
  - without warning symptoms
  - that may cause death
  The risk of getting an ulcer or bleeding increases with:
  - past history of stomach ulcers, or stomach or intestinal bleeding with use of NSAIDs
  - taking medicines called “corticosteroids”, “anticoagulants”, “SSRIs”, or “SNRIs”
  - increasing doses of NSAIDs
  - longer use of NSAIDs
  - smoking
  - drinking alcohol
  - older age
  - poor health
  - advanced liver disease
  - bleeding problems
  NSAIDs should only be used:
  - exactly as prescribed
  - at the lowest dose possible for your treatment
  - for the shortest time needed

What are NSAIDs?
NSAIDs are used to treat pain and redness, swelling, and heat (inflammation) from medical conditions such as different types of arthritis, menstrual cramps, and other types of short-term pain.

Who should not take NSAIDs?
Do not take NSAIDs:
• if you have had an asthma attack, hives, or other allergic reaction with aspirin or any other NSAIDs.
• right before or after heart bypass surgery.

Before taking NSAIDs, tell your healthcare provider about all of your medical conditions, including if you:

- have liver or kidney problems
- have high blood pressure
- have asthma
- are pregnant or plan to become pregnant. Taking NSAIDs at about 20 weeks of pregnancy or later may harm your unborn baby. If you need to take NSAIDs for more than 2 days when you are between 20 and 30 weeks of pregnancy, your healthcare provider may need to monitor the amount of fluid in your womb around your baby. You should not take NSAIDs after about 30 weeks of pregnancy.
- are breastfeeding or plan to breast feed.

Tell your healthcare provider about all of the medicines you take, including prescription or over-the-counter medicines, vitamins or herbal supplements. NSAIDs and some other medicines can interact with each other and cause serious side effects. Do not start taking any new medicine without talking to your healthcare provider first.

What are the possible side effects of NSAIDs?
NSAIDs can cause serious side effects, including:
See "What is the most important information I should know about medicines called Nonsteroidal Anti-inflammatory Drugs (NSAIDs)?"

- new or worse high blood pressure
- heart failure
- liver problems including liver failure
- kidney problems including kidney failure
- low red blood cells (anemia)
- life-threatening skin reactions
- life-threatening allergic reactions
- Other side effects of NSAIDs include: stomach pain, constipation, diarrhea, gas, heartburn, nausea, vomiting, and dizziness.

Get emergency help right away if you get any of the following symptoms:

- shortness of breath or trouble breathing
- chest pain
- weakness in one part or side of your body
- slurred speech
- swelling of the face or throat

Stop taking your NSAID and call your healthcare provider right away if you get any of the following symptoms:

- nausea
- more tired or weaker than usual
- diarrhea
- itching
- your skin or eyes look yellow
- indigestion or stomach pain
- flu-like symptoms
- vomit blood
- there is blood in your bowel movement or it is black and sticky like tar
- unusual weight gain
- skin rash or blisters with fever
- swelling of the arms, legs, hands and feet

If you take too much of your NSAID, call your healthcare provider or get medical help right away.
These are not all the possible side effects of NSAIDs. For more information, ask your healthcare provider or pharmacist about NSAIDs.
Call your doctor for medical advice about side effects. You may report side effects to FDA at 1-800-FDA-1088.

Other information about NSAIDs

- Aspirin is an NSAID but it does not increase the chance of a heart attack. Aspirin can cause bleeding in the brain, stomach, and intestines. Aspirin can also cause ulcers in the stomach and intestines.
- Some NSAIDs are sold in lower doses without a prescription (over-the-counter). Talk to your healthcare provider before using over-the-counter NSAIDs for more than 10 days.

General information about the safe and effective use of NSAIDs
Medicines are sometimes prescribed for purposes other than those listed in a Medication Guide. Do not use NSAIDs for a condition for which it was not prescribed. Do not give NSAIDs to other people, even if they have the same symptoms that you have. It may harm them.
If you would like more information about NSAIDs, talk with your healthcare provider. You can ask your pharmacist or healthcare provider for information about NSAIDs that is written for health professionals.

Distributed by: TWi Pharmaceuticals USA, Inc. Paramus, NJ 07652
For more information, call 1-844-518-2989

This Medication Guide has been approved by the U.S. Food and Drug Administration.

PKG03119
Rev. 01/2024

PACKAGE LABEL

NDC 24979-249-01 Rx Only

375 mg
NAPRELAN®
(naproxen sodium)
CONTROLLED-RELEASE TABLETS

Each tablet contains 412.5 mg naproxensodium equivalent to 375 mg naproxen

Dispense the accompanying
Medication Guide to each patient.

100 Tablets

PACKAGE LABEL

NDC 24979-250-68 Rx Only

500 mg
NAPRELAN®
(naproxen sodium)
CONTROLLED-RELEASE TABLETS

Each tablet contains 550 mg naproxensodium equivalent to 500 mg naproxen

Dispense the accompanying
Medication Guide to each patient.

75 Tablets

PACKAGE LABEL

NDC 24979-251-06 Rx Only

750 mg
NAPRELAN®
(naproxen sodium)
CONTROLLED-RELEASE TABLETS

Each tablet contains 825 mg naproxensodium equivalent to 750 mg naproxen

Dispense the accompanying
Medication Guide to each patient.

30 Tablets